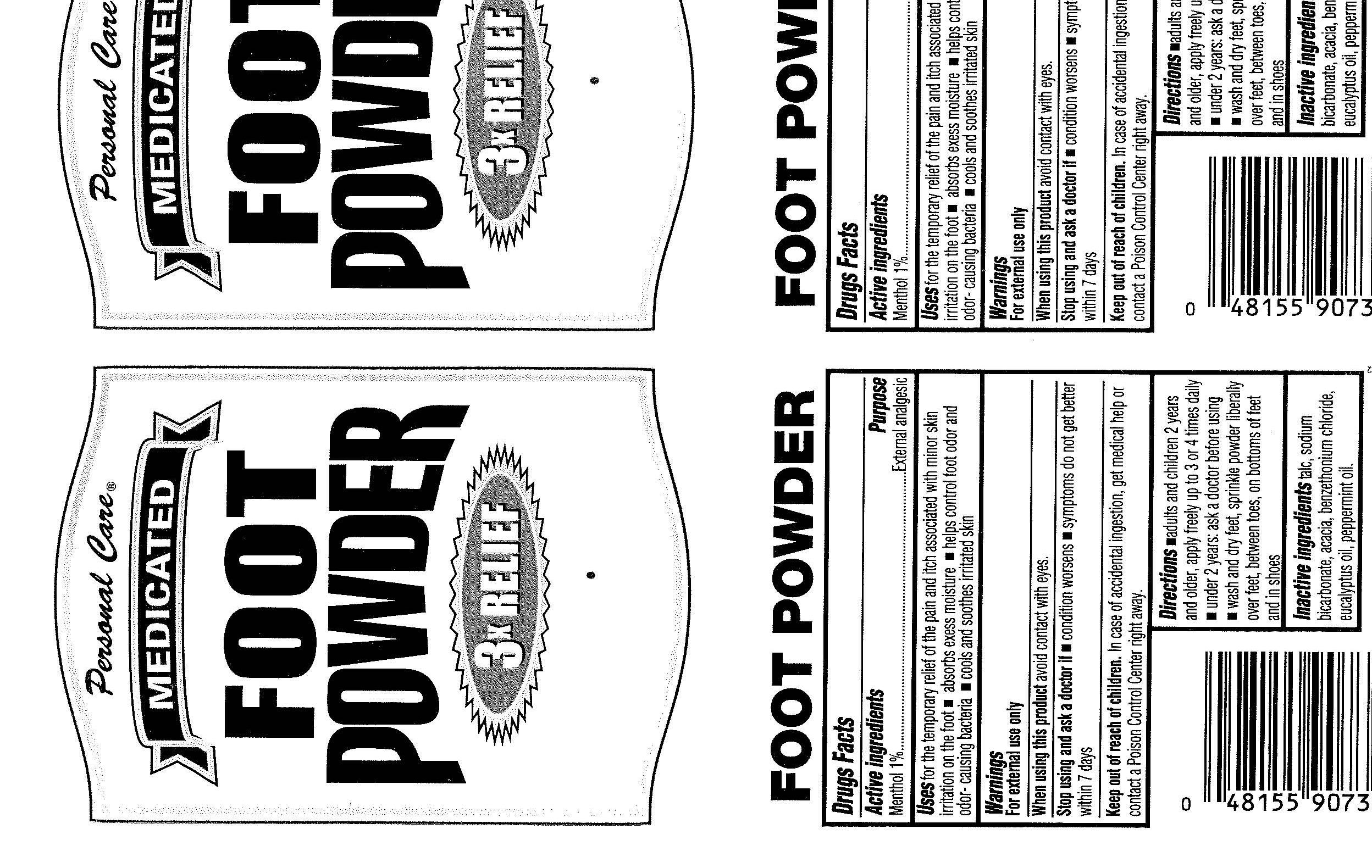 DRUG LABEL: Personal Care
NDC: 29500-9091 | Form: POWDER
Manufacturer: Personal Care Products, Inc.
Category: otc | Type: HUMAN OTC DRUG LABEL
Date: 20090907

ACTIVE INGREDIENTS: Menthol 20 mg/2 g
INACTIVE INGREDIENTS: Talc; Sodium Bicarbonate; Acacia; Benzethonium chloride; Eucalyptus Oil; Peppermint Oil

Personal Care Medicated Foot Powder

Active ingredients Purpose
Menthol 1 percent External analgesic

PURPOSE

Uses for the temporary relief of the pain and itch associated with minor skin
irritation on the foot - absorbs excess moisture - helps control foot odor and
odor-causing bacteria - cools and soothes irritated skin

Warnings
For external use only
When using this product avoid contact with eyes.

Stop using and ask a doctor if
- condition worsens - symptoms do not get better within 7 days

Keep out of reach of children. In case of accidental ingestion, get medical help or
contact a Poison Control Center right away.

Directions
- adults and children 2 years and older, apply freely up to 3 or 4 times daily
- under 2 years: ask a doctor before using
- wash and dry feet, sprinkle powder liberally over feet, between toes, on bottoms of feet, and in shoes

Inactive ingredients
talc, sodium bicarbonate, acacia, benzethonium chloride, eucalyptus oil, peppermint oil